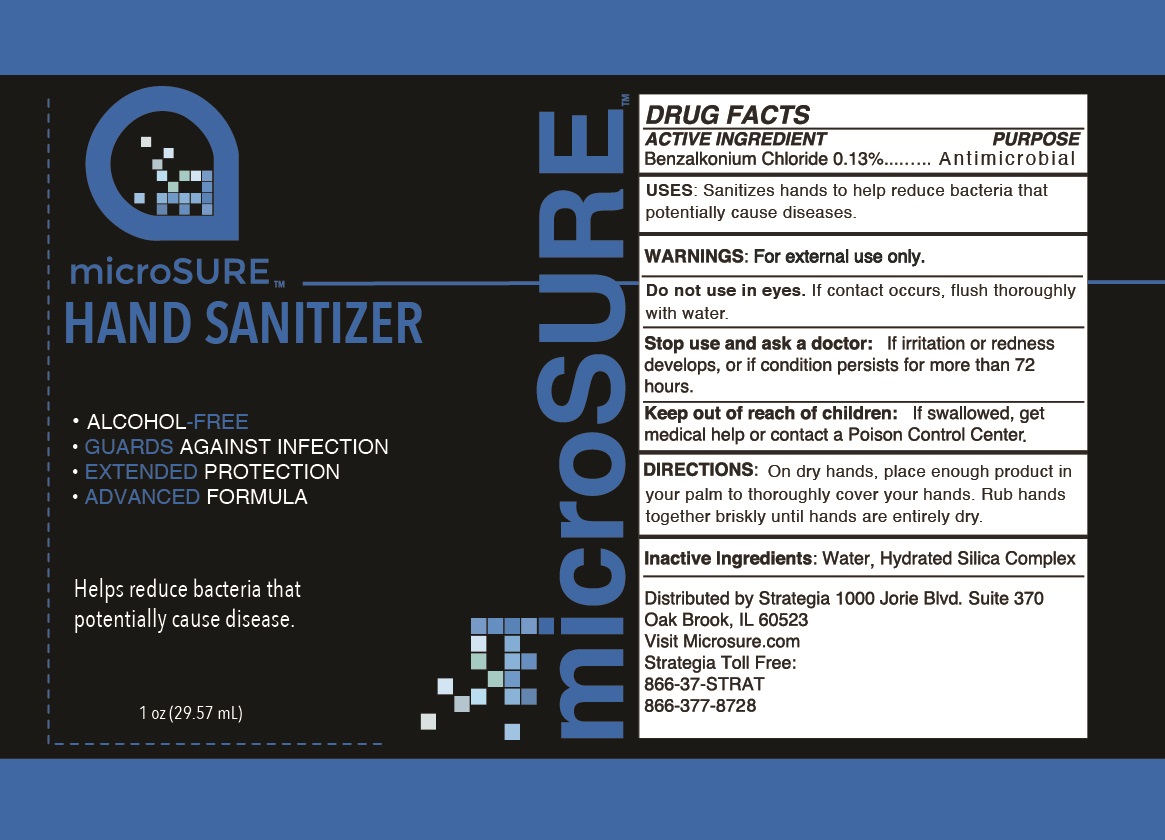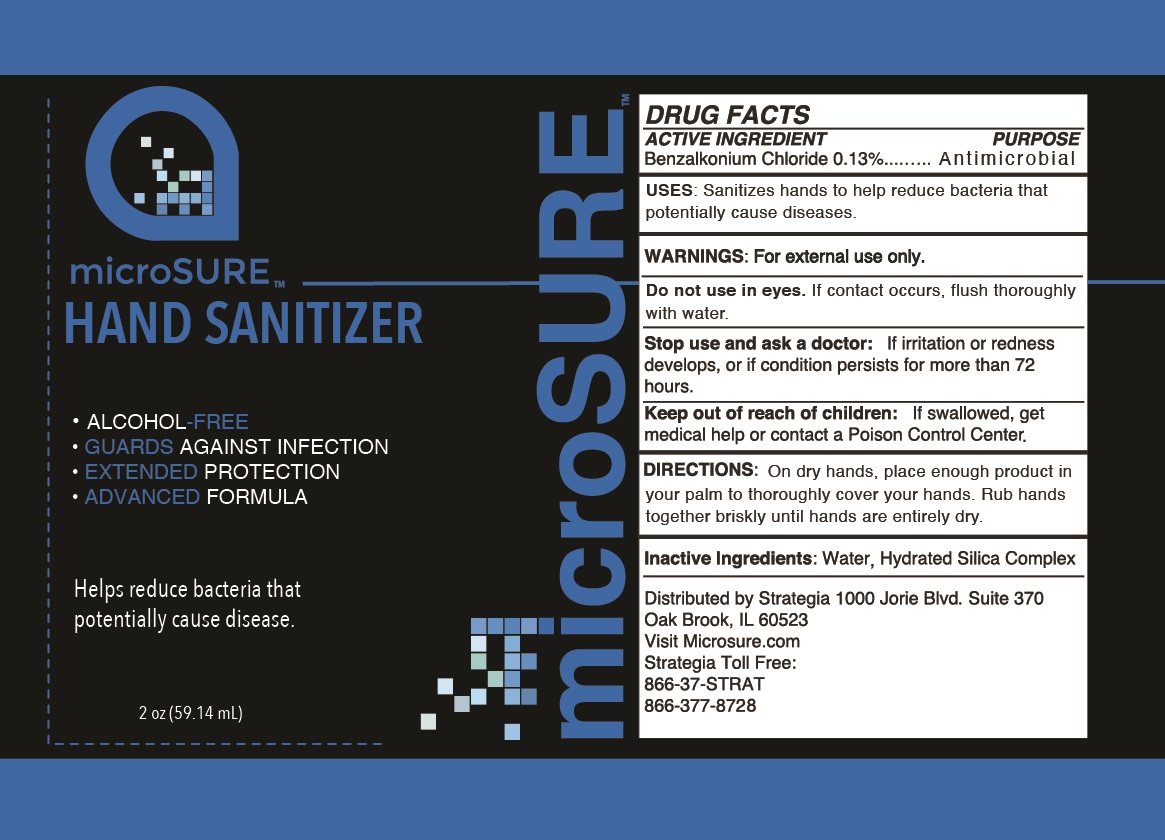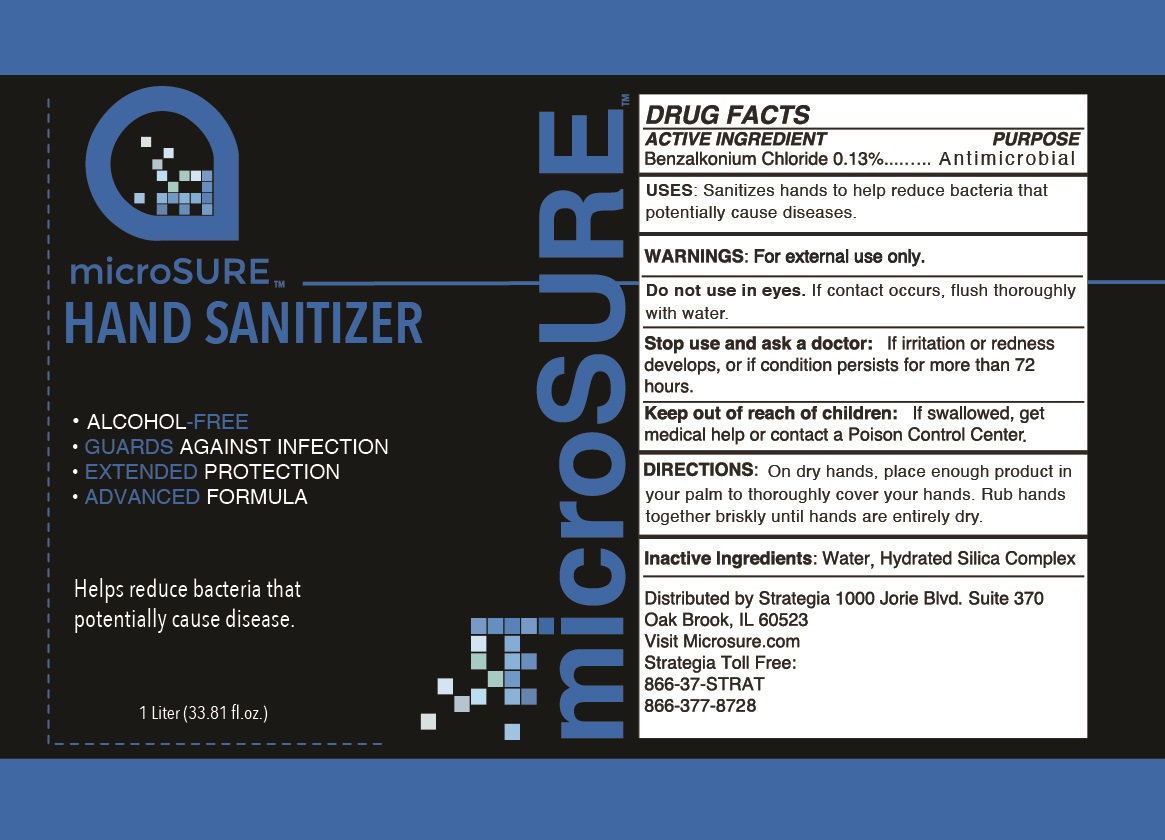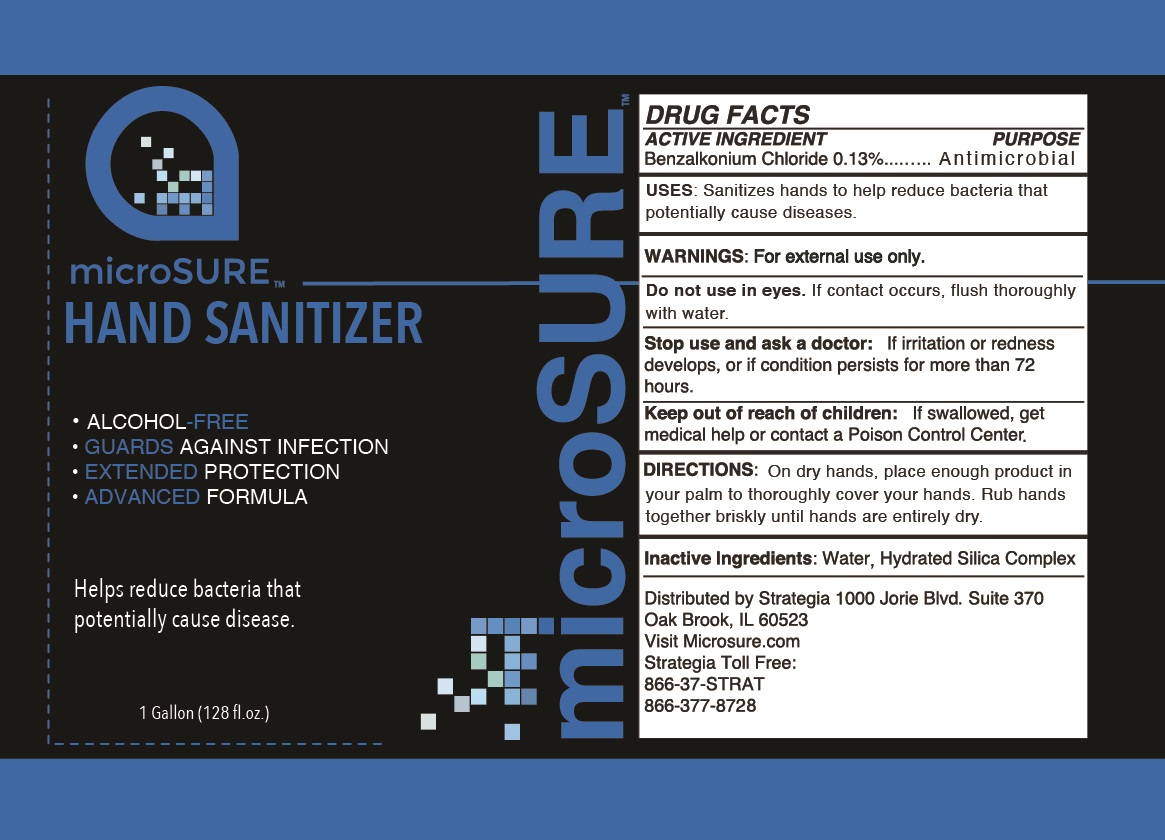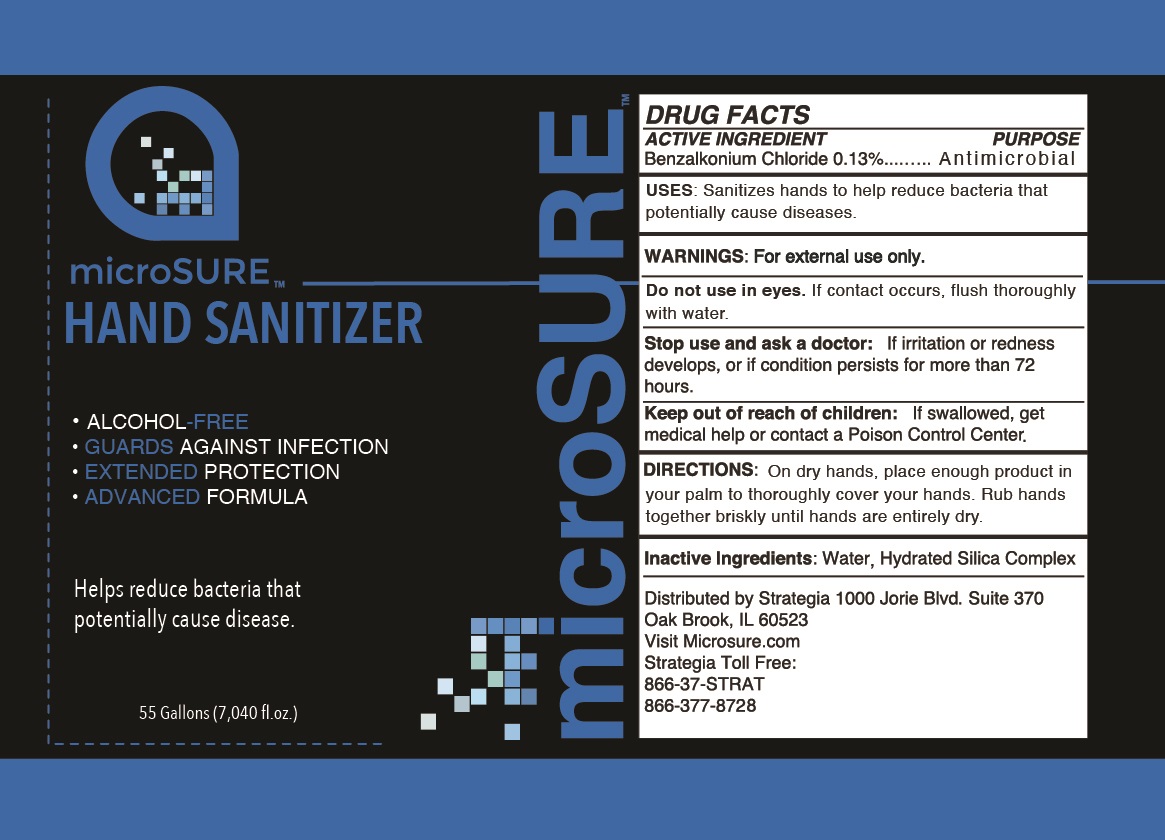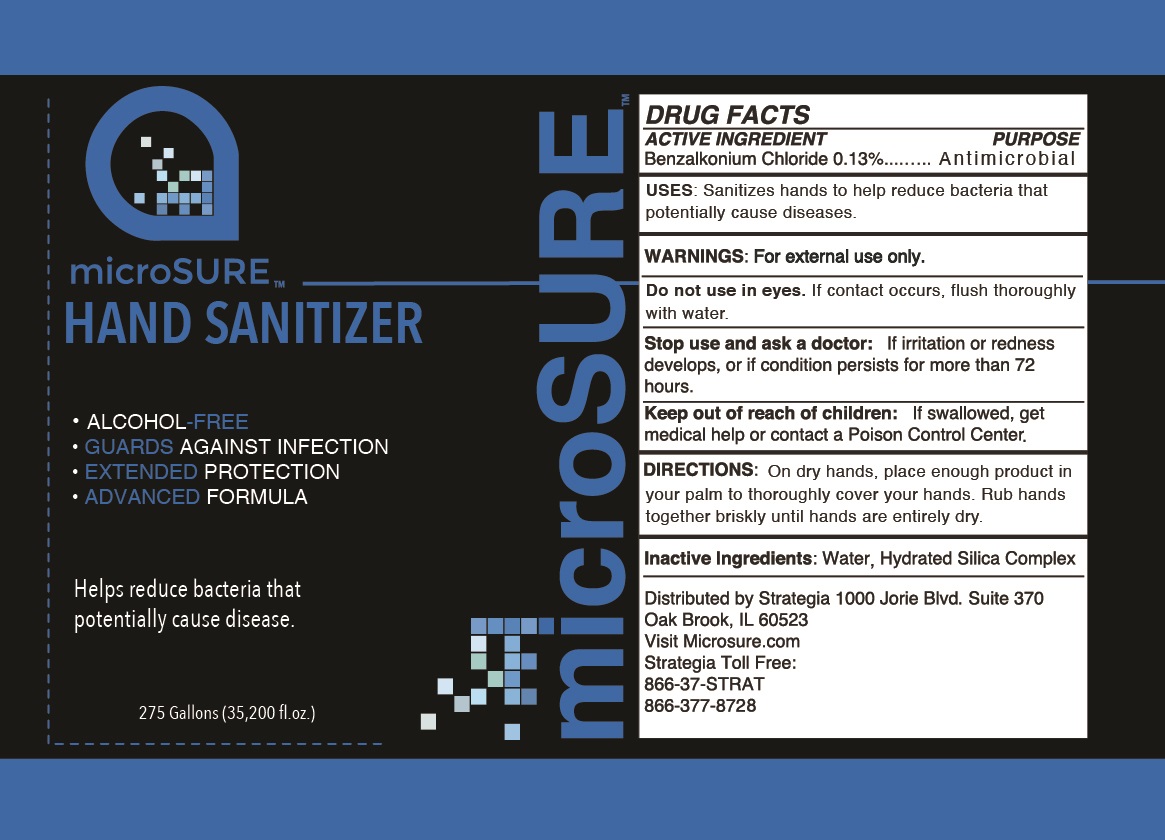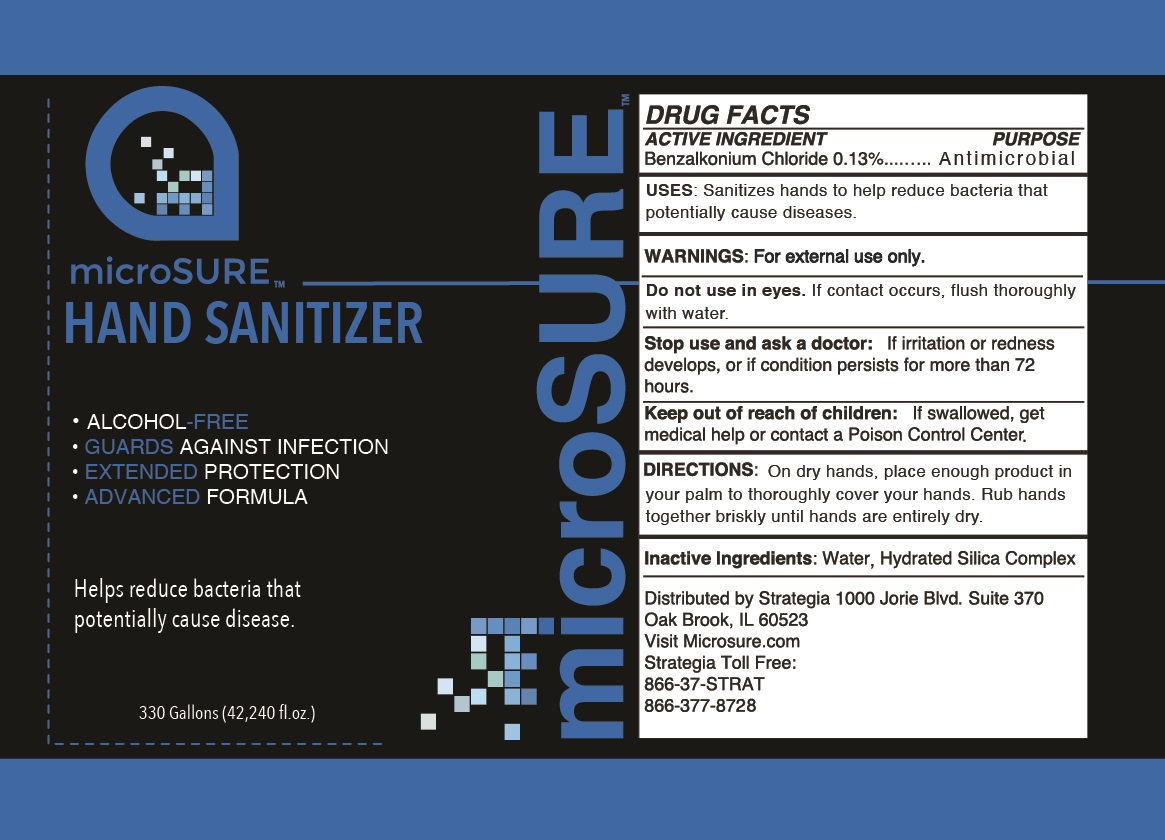 DRUG LABEL: Microsure Hand Sanitizer
NDC: 72513-000 | Form: SOLUTION
Manufacturer: Strategia Project Management, Inc.
Category: otc | Type: HUMAN OTC DRUG LABEL
Date: 20231220

ACTIVE INGREDIENTS: BENZALKONIUM CHLORIDE 1.3 mg/1 mL
INACTIVE INGREDIENTS: WATER; HYDRATED SILICA

Microsure Hand Sanitizer

ACTIVE INGREDIENT

Benzalkonium Chloride 0.13%

PURPOSE

Antimicrobial

USES:

Sanitizes hands to helps reduce bacteria that potentially cause diseases.

WARNINGS:

For external use only.

Do not use

in eyes. If contact occurs, flush thoroughly with water.

Stop use and ask a doctor:

If irritation or redness develops, or if condition persists for more than 72 hours.

Keep out of reach of children:

If swallowed, get medical help or contact a Poison Control Center.

DIRECTIONS:

Wipe on both hands to disinfect palms, between fingers, back of hands, and wrists. 8 hours of continues protection once skin is fully dry.

Inactive Ingredients:

Water, Hydrated Silica Complex